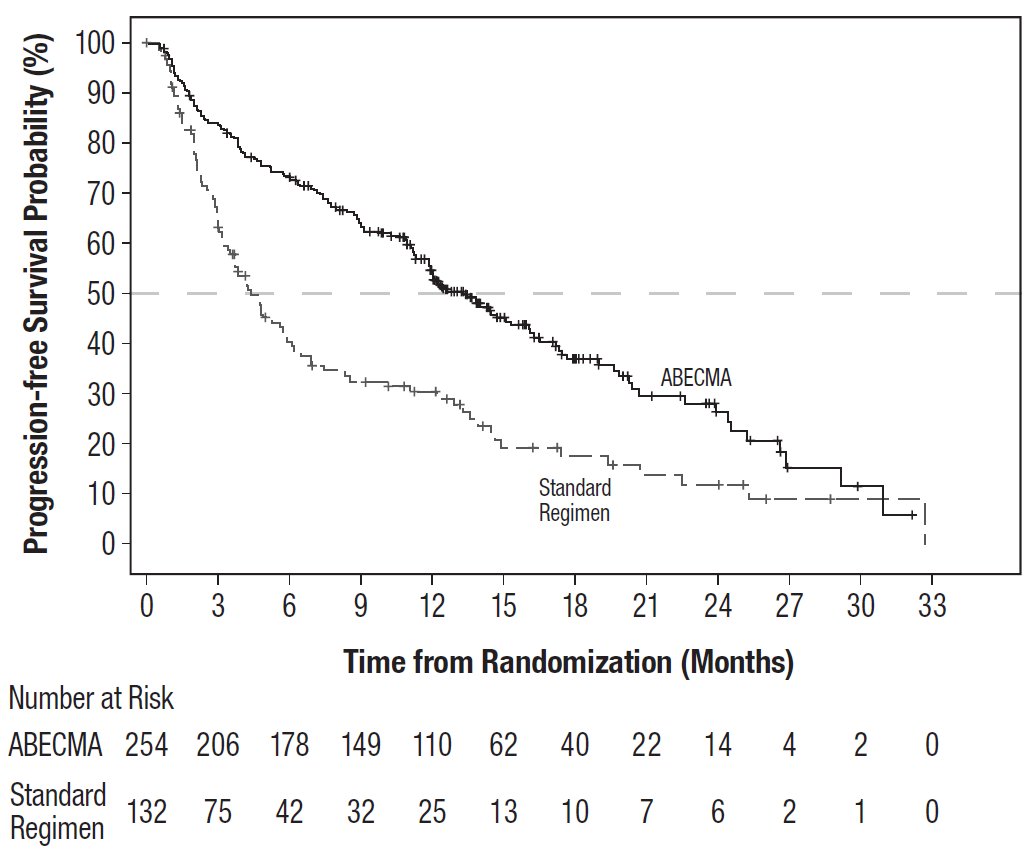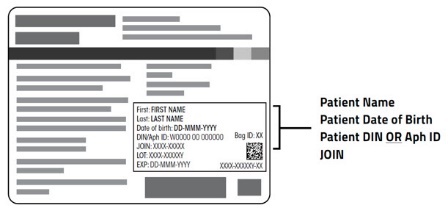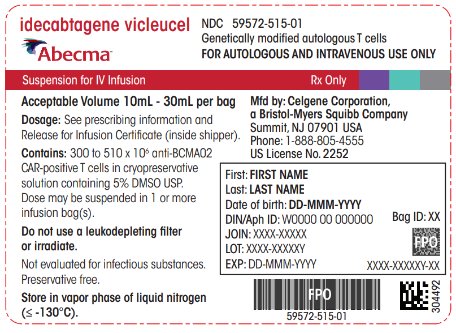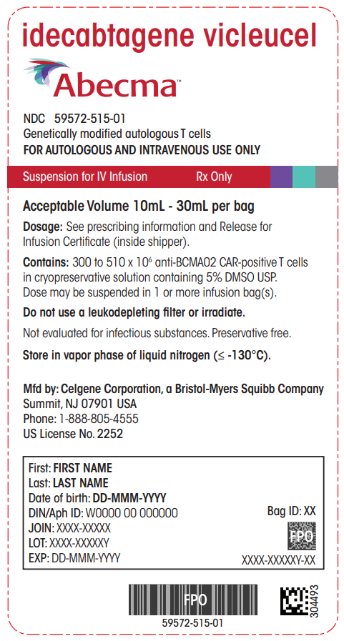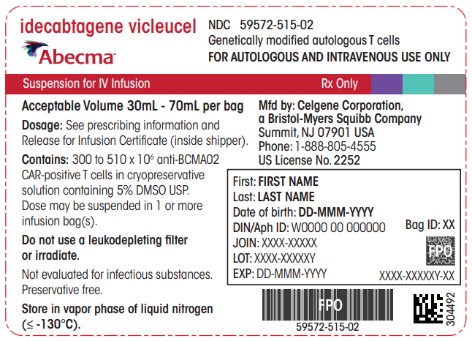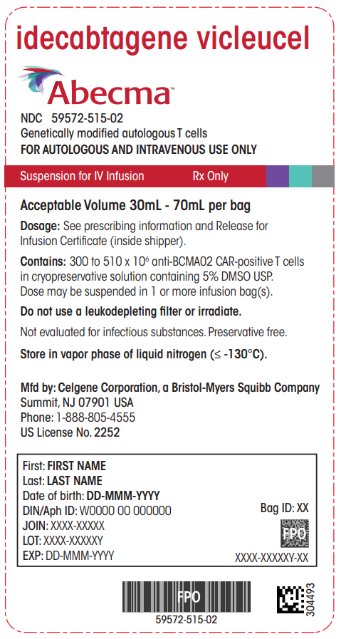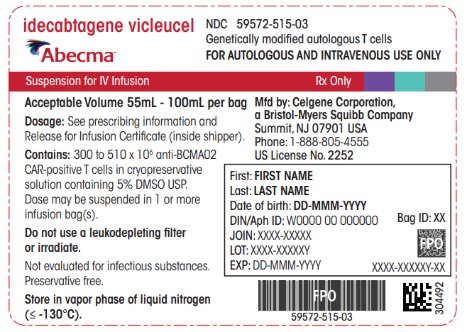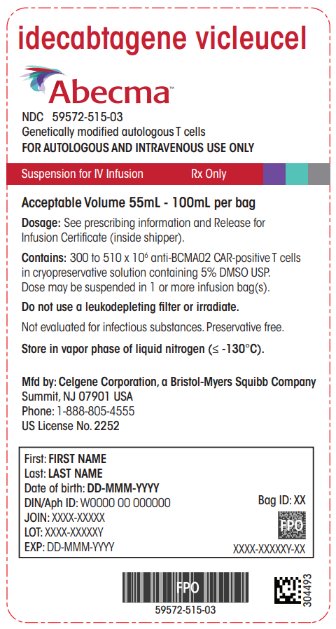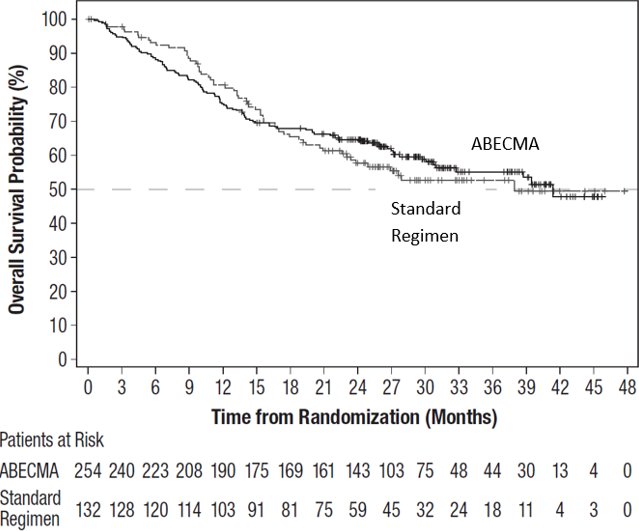 DRUG LABEL: Abecma
NDC: 59572-515 | Form: SUSPENSION
Manufacturer: Celgene Corporation
Category: other | Type: CELLULAR THERAPY
Date: 20251125

ACTIVE INGREDIENTS: IDECABTAGENE VICLEUCEL 300000000 1/1 1
INACTIVE INGREDIENTS: DIMETHYL SULFOXIDE; WATER

HIGHLIGHTS OF PRESCRIBING INFORMATION

These highlights do not include all the information needed to use ABECMA safely and effectively. See full prescribing information for ABECMA.
ABECMA® (idecabtagene vicleucel), suspension for intravenous infusion
Initial U.S. Approval: 2021

RECENT MAJOR CHANGES

Boxed Warning | 6/2025
Dosage and Administration (2.2) | 11/2025
Dosage and Administration (2.2, 2.3) | 6/2025
Warnings and Precautions (5.2, 5.3) | 6/2025
Warnings and Precautions (5.2, 5.3) | 11/2025
Warnings and Precautions, ABECMA REMS (5.5) Removed | 6/2025
Warnings and Precautions, Effects on Ability to Drive and Use Machines
(5.11) Removed | 6/2025

WARNING: CYTOKINE RELEASE SYNDROME, NEUROLOGIC TOXICITIES, HLH/MAS, PROLONGED CYTOPENIA, AND SECONDARY HEMATOLOGICAL MALIGNANCIES

See full prescribing information for complete boxed warning.

- Cytokine Release Syndrome (CRS), including fatal or life-threatening reactions, occurred in patients following treatment with ABECMA. Do not administer ABECMA to patients with active infection or inflammatory disorders. Treat severe or life-threatening CRS with tocilizumab or tocilizumab and corticosteroids. (2.2, 2.3, 5.2)
- Neurologic toxicities, which may be severe or life-threatening, occurred following treatment with ABECMA, including concurrently with CRS, after CRS resolution, or in the absence of CRS. Monitor for neurologic events after treatment with ABECMA. Provide supportive care and/or corticosteroids as needed. (2.2, 2.3, 5.3)
- Hemophagocytic Lymphohistiocytosis/Macrophage Activation Syndrome (HLH/MAS), including fatal and life-threatening reactions, occurred in patients following treatment with ABECMA. HLH/MAS can occur with CRS or neurologic toxicities. (5.4)
- Prolonged Cytopenia with bleeding and infection, including fatal outcomes following stem cell transplantation for hematopoietic recovery, occurred following treatment with ABECMA. (5.7)
- T cell malignancies have occurred following treatment of hematologic malignancies with BCMA- and CD19-directed genetically modified autologous T cell immunotherapies, including ABECMA. (5.9)

1 INDICATIONS AND USAGE

ABECMA is a B-cell maturation antigen (BCMA)-directed genetically modified autologous T cell immunotherapy indicated for the treatment of adult patients with relapsed or refractory multiple myeloma after two or more prior lines of therapy including an immunomodulatory agent, a proteasome inhibitor, and an anti-CD38 monoclonal antibody. (1)

2 DOSAGE AND ADMINISTRATION

For autologous use only. For intravenous use only.

- Do NOT use a leukodepleting filter. (2.2)
- Administer a lymphodepleting chemotherapy regimen of cyclophosphamide and fludarabine before infusion of ABECMA. (2.2)
- Confirm the patient's identity prior to infusion. (2.2)
- Premedicate with acetaminophen and an H1-antihistamine. (2.2)
- Avoid prophylactic use of dexamethasone or other systemic corticosteroids. (2.2)
- Confirm availability of tocilizumab prior to infusion. (2.2, 5.2)
- Dosing of ABECMA is based on the number of chimeric antigen receptor (CAR)-positive T cells. (2.1)
- The recommended dose range is 300 to 510 × 10^6 CAR-positive T cells. (2.1)

3 DOSAGE FORMS AND STRENGTHS

- A single dose of ABECMA contains a cell suspension of 300 to 510 × 10^6 CAR-positive T cells in one or more infusion bags. (3)

4 CONTRAINDICATIONS

None. (4)

5 WARNINGS AND PRECAUTIONS

- Hypersensitivity Reactions: Monitor for hypersensitivity reactions during infusion. (5.5)
- Infections: Monitor patients for signs and symptoms of infection; treat appropriately. (5.6)
- Prolonged Cytopenias: Patients may exhibit prolonged Grade 3 or higher cytopenias following ABECMA infusion. Monitor blood counts prior to and after ABECMA infusion. (5.7)
- Hypogammaglobulinemia: Monitor and consider immunoglobulin replacement therapy. (5.8)
- Secondary Malignancies: T cell malignancies have occurred following treatment of hematologic malignancies with BCMA- and CD19-directed genetically modified autologous T cell immunotherapies, including ABECMA. In the event that a secondary malignancy occurs after treatment with ABECMA, contact Bristol-Myers Squibb at 1-888-805-4555. (5.9)

6 ADVERSE REACTIONS

The most common nonlaboratory adverse reactions (incidence ≥20%) include pyrexia, CRS, hypogammaglobulinemia, infections–pathogen unspecified, musculoskeletal pain, fatigue, febrile neutropenia, hypotension, tachycardia, diarrhea, nausea, headache, chills, upper respiratory tract infection, encephalopathy, edema, dyspnea and viral infections. (6.1)

The most common Grade 3 or 4 laboratory adverse reactions (incidence ≥50%) include leukocyte count decreased, neutrophil count decreased, lymphocyte count decreased, platelet count decreased, and hemoglobin decreased. (6.1)

To report SUSPECTED ADVERSE REACTIONS, contact Bristol-Myers Squibb at 1-800-721-5072 or FDA at 1-800-FDA-1088 or www.fda.gov/medwatch.

FULL PRESCRIBING INFORMATION

WARNING: CYTOKINE RELEASE SYNDROME, NEUROLOGIC TOXICITIES, HLH/MAS, PROLONGED CYTOPENIA, AND SECONDARY HEMATOLOGICAL MALIGNANCIES

- Cytokine Release Syndrome (CRS), including fatal or life-threatening reactions, occurred in patients following treatment with ABECMA. Do not administer ABECMA to patients with active infection or inflammatory disorders. Treat severe or life-threatening CRS with tocilizumab or tocilizumab and corticosteroids [see Dosage and Administration (2.2, 2.3), Warnings and Precautions (5.2)].
- Neurologic toxicities, which may be severe or life-threatening, occurred following treatment with ABECMA, including concurrently with CRS, after CRS resolution, or in the absence of CRS. Monitor for neurologic events after treatment with ABECMA. Provide supportive care and/or corticosteroids as needed [see Dosage and Administration (2.2, 2.3) and Warnings and Precautions (5.3)].
- Hemophagocytic Lymphohistiocytosis/Macrophage Activation Syndrome (HLH/MAS) including fatal and life-threatening reactions, occurred in patients following treatment with ABECMA. HLH/MAS can occur with CRS or neurologic toxicities [see Warnings and Precautions (5.4)].
- Prolonged Cytopenia with bleeding and infection, including fatal outcomes following stem cell transplantation for hematopoietic recovery, occurred following treatment with ABECMA [see Warnings and Precautions (5.7)].
- T cell malignancies have occurred following treatment of hematologic malignancies with BCMA- and CD19-directed genetically modified autologous T cell immunotherapies, including ABECMA [see Warnings and Precautions (5.9)].

1 INDICATIONS AND USAGE

ABECMA is indicated for the treatment of adult patients with relapsed or refractory multiple myeloma after two or more prior lines of therapy including an immunomodulatory agent, a proteasome inhibitor, and an anti-CD38 monoclonal antibody.

2 DOSAGE AND ADMINISTRATION

2.1 Dose

For autologous use only. For intravenous use only.

ABECMA is provided as a single dose for infusion containing a suspension of chimeric antigen receptor (CAR)-positive T cells in one or more infusion bags. The recommended dose range is 300 to 510 × 10^6 CAR-positive T cells.

See the accompanying Release for Infusion Certificate (RFI Certificate) for additional information pertaining to dose [see How Supplied/Storage and Handling (16)].

2.2 Administration

ABECMA is for autologous use only. The patient's identity must match the patient identifiers on the ABECMA cassette(s) and infusion bag(s). Do not infuse ABECMA if the information on the patient-specific label(s) does not match the intended patient.

Preparing Patient for ABECMA Infusion

Confirm the availability of ABECMA prior to starting the lymphodepleting chemotherapy regimen.

Pretreatment

Administer the lymphodepleting chemotherapy regimen: cyclophosphamide 300 mg/m^2 intravenously (IV) and fludarabine 30 mg/m^2 IV for three days.

See the prescribing information of cyclophosphamide and fludarabine for information on dose adjustment in renal impairment.

Administer ABECMA two days after completion of lymphodepleting chemotherapy.

Delay the infusion of ABECMA up to seven days if a patient has any of the following conditions:

- unresolved serious adverse events (especially pulmonary events, cardiac events, or hypotension), including those after preceding chemotherapies.
- active infections or inflammatory disorders [see Warnings and Precautions (5.6)].

Premedication

Administer acetaminophen (650 mg orally) and diphenhydramine (12.5 mg IV or 25 to 50 mg orally, or another H1-antihistamine) approximately 30 to 60 minutes before infusion of ABECMA.

Avoid prophylactic use of dexamethasone or other systemic corticosteroids, as the use may interfere with the activity of ABECMA.

Receipt of ABECMA

- ABECMA is shipped directly to the cell laboratory or clinical pharmacy associated with the infusion center in the vapor phase of a liquid nitrogen shipper.
- Confirm the patient's identity with the patient identifiers on the shipper.
- If the patient is not expected to be ready for same-day administration before the shipper expires and the infusion site is qualified for onsite storage, transfer ABECMA to onsite vapor phase of liquid nitrogen storage.
- If the patient is not expected to be ready for same-day administration before the shipper expires and the infusion site is not qualified for onsite storage, contact Bristol-Myers Squibb at 1-888-805-4555 to arrange for return shipment.

Preparation of ABECMA for Infusion

1. Coordinate the timing of ABECMA thaw and infusion. Confirm the infusion time in advance and adjust the start time of the thaw of ABECMA so that it will be available for infusion when the patient is ready.
2. Prior to thawing the product, confirm that tocilizumab and emergency equipment are available prior to the infusion and during the recovery period.
3. An ABECMA dose may be contained in one or more patient-specific infusion bag(s). The infusion bag is overwrapped with a transparent plastic sleeve that is folded to the back of the infusion bag. Verify the number of bags received for the indicated dose of ABECMA prior to preparation of ABECMA for infusion.
4. Confirm patient identity: Prior to preparation of ABECMA, match the patient's identity with the patient identifiers on the ABECMA cassette(s), infusion bag(s), and the RFI Certificate.

Note: The patient identifier number may be preceded by the letters DIN or Aph ID.

5. Do not remove the ABECMA infusion bag(s) from the cassette(s) if the information on the patient-specific cassette label(s) does not match the intended patient. Contact Bristol-Myers Squibb at 1-888-805-4555 if there are any discrepancies between the labels and the patient identifiers.
6. Once patient identity is confirmed, remove the ABECMA infusion bag(s) with the overwrap sleeve from the cassette(s) and check that the patient information on the cassette label(s) matches the patient information on the bag label(s).

Figure 1: ABECMA Bag Label(s)

7. Inspect the infusion bag(s) in the overwrap sleeve for any breaches of container integrity such as breaks or cracks before thawing. If the bag(s) is compromised, do not administer and contact Bristol-Myers Squibb at 1-888-805-4555.
8. If more than one infusion bag has been received to achieve the treatment dose, thaw each infusion bag one at a time. Do not initiate thaw of the next bag until infusion of the previous bag is complete.
9. Place the infusion bag(s) inside a second sterile bag per local guidelines.
10. Thaw ABECMA infusion bag(s) in the overwrap at approximately 37°C using an approved thaw device or water bath until there is no visible ice in the infusion bag. Gently mix the contents of the bag to disperse visible clumps of cellular material. Small clumps of cellular material may persist despite gentle manual mixing. Do not wash, spin down, and/or resuspend ABECMA in new media prior to infusion.
11. Remove the infusion bag from the overwrap by unfolding the plastic sleeve at the back to expose the infusion bag. Gently pull the infusion bag out of the overwrap.
12. ABECMA should be administered within one hour of the initiation of the thaw process. ABECMA is stable for two hours at room temperature once thawed.

ABECMA Administration

- For autologous use only.
- Do NOT use a leukodepleting filter.
- Confirm tocilizumab and emergency equipment are available prior to infusion and during the recovery period.
- Central venous access may be utilized for the infusion of ABECMA and is encouraged in patients with poor peripheral access.
1. Confirm that the patient's identity matches the patient identifiers on the ABECMA infusion bag(s).
2. Prime the tubing of the infusion set with normal saline prior to infusion. An infusion set with an in-line filter (non-leukodepleting filter with a pore size range of 170 to 260 µm) can be used for thawed products with visible clumps of cellular material that do not disperse after gentle manual mixing.
3. Infuse the entire contents of the ABECMA infusion bag within one hour after start of thaw by gravity flow.
4. After the entire content of the infusion bag is infused, rinse the tubing, inclusive of the in-line filter if used, with 30 to 60 mL of normal saline at the same infusion rate to ensure as many cells as possible are infused into the patient.
5. If more than one infusion bag is received, administer all bags as directed, following steps 1-4 for each bag. Do not initiate thaw of the next bag until infusion of the previous bag is complete.

ABECMA contains human blood cells that are genetically modified with replication-incompetent, self-inactivating lentiviral vector. Follow universal precautions and local biosafety guidelines for handling and disposal of ABECMA to avoid potential transmission of infectious diseases.

Monitoring

- Monitor patients at least daily for seven days following ABECMA infusion for signs and symptoms of CRS and neurologic toxicities [see Warnings and Precautions (5.2, 5.3)].
- Instruct patients to remain within proximity of a healthcare facility for at least one week following infusion.
- Advise patients to avoid driving for at least one week following infusion.

2.3 Management of Severe Adverse Reactions

Cytokine Release Syndrome (CRS)

Identify CRS based on clinical presentation [see Warnings and Precautions (5.2)]. Evaluate for and treat other causes of fever, hypoxia, and hypotension.

If CRS is suspected, manage according to the recommendations in Table 1. Physicians may also consider management per current practice guidelines.

Patients who experience CRS should be closely monitored for cardiac and organ function until resolution of symptoms. Consider antiseizure prophylaxis with levetiracetam in patients who experience CRS.

Patients who experience Grade 2 or higher CRS (e.g., hypotension not responsive to fluids, or hypoxia requiring supplemental oxygenation) should be monitored with continuous cardiac telemetry and pulse oximetry.

For severe or life-threatening CRS, consider intensive care unit level monitoring and supportive therapy.

For CRS refractory to first line interventions such as tocilizumab or tocilizumab and corticosteroids, consider alternate treatment options (i.e., higher corticosteroid dose, alternative anti-cytokine agents, anti-T cell therapies). Refractory CRS is characterized by fevers, end-organ toxicity (e.g., hypoxia, hypotension) not improving within 12 hours of first line interventions or development of hemophagocytic lymphohistiocytosis/macrophage activation syndrome (HLH/MAS).

If concurrent neurologic toxicity is suspected during CRS, administer:

- Corticosteroids according to the more aggressive intervention based on the CRS and neurologic toxicity grades in Tables 1 and 2
- Tocilizumab according to the CRS grade in Table 1
- Antiseizure medication according to the neurologic toxicity in Table 2

Table 1: CRS Grading and Management Guidance
CRS Gradea | Tocilizumabb | Corticosteroidsc
Grade 1 Symptoms require symptomatic treatment only (e.g., fever, nausea, fatigue, headache, myalgia, malaise). | If onset 72 hours or more after infusion, treat symptomatically.; If onset less than 72 hours after infusion, consider tocilizumab 8 mg/kg IV over 1 hour (not to exceed 800 mg). | Consider dexamethasone 10 mg IV every 24 hours.
Grade 2 Symptoms require and respond to moderate intervention.; Oxygen requirement less than 40% FiO2 or hypotension responsive to fluids, or low dose of one vasopressor, or Grade 2 organ toxicity. | Administer tocilizumab 8 mg/kg IV over 1 hour (not to exceed 800 mg). Repeat tocilizumab every 8 hours as needed if not responsive to intravenous fluids or increasing supplemental oxygen.; Limit to a maximum of 3 doses in a 24-hour period; maximum total of 4 doses. | Consider dexamethasone 10 mg IV every 12-24 hours.
Grade 2 Symptoms require and respond to moderate intervention.; Oxygen requirement less than 40% FiO2 or hypotension responsive to fluids, or low dose of one vasopressor, or Grade 2 organ toxicity. | If no improvement within 24 hours or rapid progression, repeat tocilizumab and escalate dose and frequency of dexamethasone (20 mg IV every 6 to 12 hours).; If no improvement within 24 hours or continued rapid progression, switch to methylprednisolone 2 mg/kg followed by 2 mg/kg divided 4 times per day.; After 2 doses of tocilizumab, consider alternative anti-cytokine agents. Do not exceed 3 doses of tocilizumab in 24 hours, or 4 doses in total.
Grade 3 Symptoms require and respond to aggressive intervention.; Fever, oxygen requirement ≥40% FiO2, or hypotension requiring high-dose or multiple vasopressors, or Grade 3 organ toxicity or Grade 4 transaminitis. | Per Grade 2 | Administer dexamethasone 10 mg IV every 12 hours.
Grade 3 Symptoms require and respond to aggressive intervention.; Fever, oxygen requirement ≥40% FiO2, or hypotension requiring high-dose or multiple vasopressors, or Grade 3 organ toxicity or Grade 4 transaminitis. | If no improvement within 24 hours or rapid progression, repeat tocilizumab and escalate dose and frequency of dexamethasone (20 mg IV every 6 to 12 hours). If no improvement within 24 hours or continued rapid progression, switch to methylprednisolone 2 mg/kg followed by 2 mg/kg divided 4 times per day.; After 2 doses of tocilizumab, consider alternative anti-cytokine agents.; Do not exceed 3 doses of tocilizumab in 24 hours, or 4 doses in total.
Grade 4 Life-threatening symptoms.; Requirements for ventilator support, continuous veno-venous hemodialysis (CVVHD), or Grade 4 organ toxicity (excluding transaminitis). | Per Grade 2 | Administer dexamethasone 20 mg IV every 6 hours.
Grade 4 Life-threatening symptoms.; Requirements for ventilator support, continuous veno-venous hemodialysis (CVVHD), or Grade 4 organ toxicity (excluding transaminitis). | After 2 doses of tocilizumab, consider alternative anti-cytokine agents. Do not exceed 3 doses of tocilizumab in 24 hours, or 4 doses in total.; If no improvement within 24 hours, consider methylprednisolone (1-2 g, repeat every 24 hours if needed; taper as clinically indicated) or other anti-T cell therapies.

a Lee criteria for grading CRS (Lee et al., 2014).
b Refer to tocilizumab Prescribing Information for details.
c If corticosteroids are initiated, continue corticosteroids for at least 3 doses, and taper over a maximum of seven days.

Neurologic Toxicity

Monitor patients for signs and symptoms of neurologic toxicities (Table 2). Rule out other causes of neurologic signs or symptoms. Provide intensive care supportive therapy for severe or life-threatening neurologic toxicities. If neurologic toxicity is suspected, manage according to the recommendations in Table 2. Physicians may also consider management per current practice guidelines.

If concurrent CRS is suspected during the neurologic toxicity event, administer:

- Corticosteroids according to the more aggressive intervention based on the CRS and neurologic toxicity grades in Tables 1 and 2
- Tocilizumab according to CRS grade in Table 1
- Antiseizure medication according to neurologic toxicity in Table 2

Table 2: Neurologic Toxicity Grading and Management Guidance
Neurologic Toxicity Gradea | Corticosteroids and Antiseizure Medications
Grade 1 | Start non-sedating, antiseizure medicines (e.g., levetiracetam) for seizure prophylaxis. If 72 hours or more after infusion, observe patient. If less than 72 hours after infusion, consider dexamethasone 10 mg IV every 12 to 24 hours for 2 to 3 days.
Grade 2 | Start non-sedating, antiseizure medicines (e.g., levetiracetam) for seizure prophylaxis. Start dexamethasone 10 mg IV every 12 hours for 2-3 days, or longer for persistent symptoms. Consider taper for a total corticosteroid exposure of >3 days. Corticosteroids are not recommended for isolated Grade 2 headaches. If no improvement after 24 hours or worsening of neurologic toxicity, increase the dose and/or frequency of dexamethasone up to a maximum of 20 mg IV every 6 hours.
Grade 3 | Start non-sedating, antiseizure medicines (e.g., levetiracetam) for seizure prophylaxis. Start dexamethasone 10 to 20 mg IV every 6 to 12 hours. Corticosteroids are not recommended for isolated Grade 3 headaches. If no improvement after 24 hours or worsening of neurologic toxicity, escalate to methylprednisolone (2 mg/kg loading dose, followed by 2 mg/kg divided into 4 times a day; taper within 7 days). If cerebral edema is suspected, consider hyperventilation and hyperosmolar therapy. Give high-dose methylprednisolone (1-2 g, repeat every 24 hours if needed; taper as clinically indicated) and cyclophosphamide 1.5 g/m^2.
Grade 4 | Start non-sedating, antiseizure medicines (e.g., levetiracetam) for seizure prophylaxis. Start dexamethasone 20 mg IV every 6 hours. If no improvement after 24 hours or worsening of neurologic toxicity, escalate to high-dose methylprednisolone (1-2 g, repeat every 24 hours if needed; taper as clinically indicated). If cerebral edema is suspected, consider hyperventilation and hyperosmolar therapy. Give high-dose methylprednisolone (1-2 g, repeat every 24 hours if needed; taper as clinically indicated), and cyclophosphamide 1.5 g/m^2.
a NCI CTCAE criteria for grading neurologic toxicities version 4.03.

3 DOSAGE FORMS AND STRENGTHS

A single dose of ABECMA contains a cell suspension of 300 to 510 × 10^6 chimeric antigen receptor (CAR)-positive T cells in one or more infusion bags [see How Supplied/Storage and Handling (16)].

4 CONTRAINDICATIONS

None.

5 WARNINGS AND PRECAUTIONS

5.1 Early Death

In Study 1, a randomized (2:1), controlled trial, a higher proportion of patients experienced death within nine months after randomization in the ABECMA arm (45/254; 18%) compared to the standard regimens arm (15/132; 11%) [see Clinical Studies (14)]. Early deaths occurred in 8% (20/254) and 0% prior to ABECMA infusion and standard regimen administration, respectively, and 10% (25/254) and 11% (15/132) after ABECMA infusion and standard regimen administration, respectively. Out of the 20 deaths that occurred prior to ABECMA infusion, 15 occurred from disease progression, 3 occurred from adverse events and 2 occurred from unknown causes. Out of the 25 deaths that occurred after ABECMA infusion, 10 occurred from disease progression, 11 occurred from adverse events, and 4 occurred from unknown causes.

5.2 Cytokine Release Syndrome (CRS)

CRS, including fatal or life-threatening reactions, occurred following treatment with ABECMA. Among patients receiving ABECMA for relapsed or refractory multiple myeloma in Study 1 and Study 2 (N=349), CRS occurred in 89% (310/349), including ≥ Grade 3 CRS (Lee grading system) in 7% (23/349) of patients and Grade 5 CRS in 0.9% (3/349) of patients. The median time-to-onset of CRS, any grade, was 1 day (range: 1 to 27 days), and the median duration of CRS was 5 days (range: 1 to 63 days). In the pooled studies, the rate of ≥ Grade 3 CRS was 10% (7/71) for patients treated in dose range of 460 to 510 × 10^6 CAR-positive T cells and 5.4% (13/241) for patients treated in dose range of 300 to 460 × 10^6 CAR-positive T cells.

The most common manifestations of CRS (≥10%) included pyrexia (87%), hypotension (30%), tachycardia (26%), chills (19%), and hypoxia (16%). Grade 3 or higher events that may be associated with CRS include hypotension, hypoxia, hyperbilirubinemia, hypofibrinogenemia, ARDS, atrial fibrillation, hepatocellular injury, metabolic acidosis, pulmonary edema, coagulopathy, renal failure, multiple organ dysfunction syndrome and hemophagocytic lymphohistiocytosis/macrophage activation syndrome (HLH/MAS) [see Adverse Reactions (6.1)].

Identify CRS based on clinical presentation. Evaluate for and treat other causes of fever, hypoxia, and hypotension. CRS has been reported to be associated with findings of HLH/MAS, and the physiology of the syndromes may overlap. HLH/MAS is a potentially life-threatening condition. In patients with progressive symptoms of CRS or refractory CRS despite treatment, evaluate for evidence of HLH/MAS. Please see Section 5.4; Hemophagocytic Lymphohistiocytosis/Macrophage Activation Syndrome.

Of the 349 patients who received ABECMA in clinical trials, 226 (65%) patients received tocilizumab; 39% (135/349) received a single dose, while 26% (91/349) received more than 1 dose of tocilizumab. Overall, 24% (82/349) of patients received at least 1 dose of corticosteroids for treatment of CRS. Almost all patients who received corticosteroids for CRS also received tocilizumab. For patients treated in dose range of 460 to 510 × 10^6 CAR-positive T cells, 76% (54/71) of patients received tocilizumab and 35% (25/71) received at least 1 dose of corticosteroids for treatment of CRS. For patients treated in dose range of 300 to 460 × 10^6 CAR-positive T cells, 63% (152/241) of patients received tocilizumab and 20% (49/241) received at least 1 dose of corticosteroid for treatment of CRS.

Ensure that a minimum of two doses of tocilizumab are available prior to infusion of ABECMA.

Monitor patients at least daily for seven days following ABECMA infusion for signs and symptoms of CRS. Continue to monitor patients for signs or symptoms of CRS for at least one week after infusion. At the first sign of CRS, institute treatment with supportive care, tocilizumab and/or corticosteroids as indicated [see Dosage and Administration (2.2), (2.3)].

Counsel patients to seek immediate medical attention should signs or symptoms of CRS occur at any time [see Patient Counseling Information (17)].

5.3 Neurologic Toxicities

Neurologic toxicities, including immune-effector cell-associated neurotoxicity (ICANS), which may be severe or life-threatening, occurred concurrently with CRS, after CRS resolution, or in the absence of CRS following treatment with ABECMA.

In patients receiving ABECMA in Study 1 and Study 2, CAR T cell-associated neurotoxicity occurred in 40% (139/349), including Grade 3 in 4% (14/349) and Grade 4 in 0.6% (2/349) of patients. The median time to onset of neurotoxicity was 2 days (range: 1 to 148 days). The median duration of CAR T cell-associated neurotoxicity was 8 days (range: 1 to 720 days) in all patients including those with ongoing neurologic events at the time of death or data cut off. CAR T cell-associated neurotoxicity resolved in 123 of 139 (88%) patients and median time to resolution was 5 days (range: 1 to 245 days). One-hundred and thirty four out of 349 (38%) patients with neurotoxicity had CRS. The onset of neurotoxicity during CRS was observed in 93 patients, before the onset of CRS in 12 patients, and after the CRS event in 29 patients. The rate of Grade 3 or 4 CAR T cell-associated neurotoxicity was 5.6% (4/71) and 3.7% (9/241) for patients treated in dose range of 460 to 510 × 10^6 CAR-positive T cells and 300 to 460 × 10^6 CAR-positive T cells, respectively. The most frequent (≥5%) manifestations of CAR T cell-associated neurotoxicity include encephalopathy (21%), headache (15%), dizziness (8%), delirium (6%), and tremor (6%).

At the safety update for Study 1, one patient developed fatal neurotoxicity 43 days after ABECMA. In Study 2, one patient had ongoing Grade 2 neurotoxicity at the time of death. Two patients had ongoing Grade 1 tremor at the time of data cutoff.

Cerebral edema has been associated with ABECMA in a patient in another study in multiple myeloma. Grade 3 myelitis and Grade 3 parkinsonism have occurred after treatment with ABECMA in another study in multiple myeloma.

Monitor patients at least daily for seven days following ABECMA infusion for signs and symptoms of neurologic toxicities. Rule out other causes of neurologic symptoms. Continue to monitor patients for signs or symptoms of neurologic toxicities for at least one week after infusion and treat promptly. Neurologic toxicity should be managed with supportive care and/or corticosteroids as needed [see Dosage and Administration (2.2), (2.3)]. Advise patients to avoid driving for at least one week following infusion.

Counsel patients to seek immediate medical attention should signs or symptoms of neurologic toxicity occur at any time [see Patient Counseling Information (17)].

5.4 Hemophagocytic Lymphohistiocytosis (HLH)/Macrophage Activation Syndrome (MAS)

In patients receiving ABECMA in Study 1 and Study 2, HLH/MAS occurred in 2.9% (10/349) of patients. All events of HLH/MAS had onset within 10 days of receiving ABECMA, with a median onset of 6.5 days (range: 4 to 10 days) and occurred in the setting of ongoing or worsening CRS. Five patients with HLH/MAS had overlapping neurotoxicity. The manifestations of HLH/MAS include hypotension, hypoxia, multiple organ dysfunction, renal dysfunction, and cytopenia.

In Study 1, one patient had Grade 5, two patients had Grade 4 and two patients had Grade 3 HLH/MAS. The patient with Grade 5 HLH/MAS also had Grade 5 candida sepsis and Grade 5 CRS. In another patient who died due to stroke, the Grade 4 HLH/MAS had resolved prior to death. Two cases of Grade 3 and one case of Grade 4 HLH/MAS had resolved.

In Study 2, one patient treated in the 300 × 10^6 CAR-positive T cells dose cohort developed fatal multi-organ HLH/MAS with CRS. In another patient with fatal bronchopulmonary aspergillosis, HLH/MAS was contributory to the fatal outcome. Three cases of Grade 2 HLH/MAS resolved.

HLH/MAS is a potentially life-threatening condition with a high mortality rate if not recognized early and treated. Treatment of HLH/MAS should be administered per institutional standards.

5.5 Hypersensitivity Reactions

Allergic reactions may occur with the infusion of ABECMA. Serious hypersensitivity reactions, including anaphylaxis, may be due to dimethyl sulfoxide (DMSO) in ABECMA.

5.6 Infections

ABECMA should not be administered to patients with active infections or inflammatory disorders. Severe, life‑threatening, or fatal infections occurred in patients after ABECMA infusion.

In all patients receiving ABECMA in Study 1 and Study 2, infections (all grades) occurred in 61% of patients. Grade 3 or 4 infections occurred in 21% of patients. Grade 3 or 4 infections with an unspecified pathogen occurred in 12%, viral infections in 7%, bacterial infections in 4.3%, and fungal infections in 1.4% of patients. Overall, 15 patients had Grade 5 infections (4.3%); 8 patients (2.3%) with infections of pathogen unspecified, 3 patients (0.9%) with fungal infections, 3 patients (0.9%) with viral infections, and 1 patient (0.3%) with bacterial infection.

Monitor patients for signs and symptoms of infection before and after ABECMA infusion and treat appropriately. Administer prophylactic, pre-emptive, and/or therapeutic antimicrobials according to standard institutional guidelines.

Febrile neutropenia was observed in 38% (133/349) of patients after ABECMA infusion and may be concurrent with CRS. In the event of febrile neutropenia, evaluate for infection and manage with broad-spectrum antibiotics, fluids, and other supportive care as medically indicated.

Viral Reactivation

Cytomegalovirus (CMV) infection resulting in pneumonia and death has occurred following ABECMA administration. Monitor and treat for CMV reactivation in accordance with clinical guidelines.

Hepatitis B virus (HBV) reactivation, in some cases resulting in fulminant hepatitis, hepatic failure, and death, can occur in patients treated with drugs directed against plasma cells.

Perform screening for CMV, HBV, hepatitis C virus (HCV), and human immunodeficiency virus (HIV) in accordance with clinical guidelines before collection of cells for manufacturing.

Consider antiviral therapy to prevent viral reactivation per local institutional guidelines/clinical practice.

5.7 Prolonged Cytopenias

Patients may exhibit prolonged cytopenias following lymphodepleting chemotherapy and ABECMA infusion.

In patients receiving ABECMA in Study 1 and Study 2, 40% of patients (139/349) experienced prolonged Grade 3 or 4 neutropenia and 42% (145/349) experienced prolonged Grade 3 or 4 thrombocytopenia that had not resolved by Month 1 following ABECMA infusion. In 89% (123/139) of patients who recovered from Grade 3 or 4 neutropenia after Month 1, the median time to recovery from ABECMA infusion was 1.9 months. In 76% (110/145) of patients who recovered from Grade 3 or 4 thrombocytopenia, the median time to recovery was 1.9 months. Five patients underwent stem cell therapy for hematopoietic reconstitution due to prolonged cytopenia. The rate of Grade 3 or 4 thrombocytopenia was 62% (44/71) and 56% (135/241) for patients treated in dose range of 460 to 510 × 10^6 CAR-positive T cells and 300 to 460 × 10^6 CAR-positive T cells, respectively.

Monitor blood counts prior to and after ABECMA infusion. Manage cytopenia with myeloid growth factor and blood product transfusion support according to local institutional guidelines.

5.8 Hypogammaglobulinemia

Plasma cell aplasia and hypogammaglobulinemia can occur in patients receiving treatment with ABECMA.

In all patients receiving ABECMA in Study 1 and Study 2, hypogammaglobulinemia was reported as an adverse event in 13% (46/349) of patients; laboratory IgG levels fell below 500 mg/dL after infusion in 37% (130/349) of patients treated with ABECMA.

Hypogammaglobulinemia either as an adverse reaction or laboratory IgG level below 500 mg/dL after infusion occurred in 45% (158/349) of patients treated with ABECMA. Forty-one percent of patients received intravenous immunoglobulin (IVIG) post-ABECMA for serum IgG <400 mg/dL.

Monitor immunoglobulin levels after treatment with ABECMA and administer IVIG for IgG <400 mg/dL. Manage per local institutional guidelines, including infection precautions and antibiotic or antiviral prophylaxis.

Use of Live Vaccines

The safety of immunization with live viral vaccines during or following ABECMA treatment has not been studied. Vaccination with live virus vaccines is not recommended for at least six weeks prior to the start of lymphodepleting chemotherapy, during ABECMA treatment, and until immune recovery following treatment with ABECMA.

5.9 Secondary Malignancies

Patients treated with ABECMA may develop secondary malignancies. In Study 1, myeloid neoplasms (four cases of myelodysplastic syndrome and one case of acute myeloid leukemia) occurred in 2.2% (5/222) of patients following treatment with ABECMA compared to none in the standard regimens arm at the time of the safety update. The median time to onset of myeloid neoplasm from ABECMA infusion was 338 days (Range: 277 to 794 days). Three of these five patients have died following the development of myeloid neoplasm. One out of the five cases of myeloid neoplasm occurred after initiation of subsequent antimyeloma therapy.

T cell malignancies have occurred following treatment of hematologic malignancies with BCMA- and CD19‑directed genetically modified autologous T cell immunotherapies, including ABECMA. Mature T cell malignancies, including CAR-positive tumors, may present as soon as weeks following infusion, and may include fatal outcomes [see Boxed Warning, Adverse Reactions (6.3), Patient Counseling Information (17)].

Monitor life-long for secondary malignancies. In the event that a secondary malignancy occurs, contact
Bristol-Myers Squibb at 1‑888‑805‑4555 for reporting and to obtain instructions on collection of patient samples for testing of secondary malignancy.

6 ADVERSE REACTIONS

The following adverse reactions are described elsewhere in the labeling:

- Early Death [see Warnings and Precautions (5.1), Clinical Studies (14)]
- Cytokine Release Syndrome [see Warnings and Precautions (5.2)]
- Neurologic Toxicities [see Warnings and Precautions (5.3)]
- Hemophagocytic Lymphohistiocytosis (HLH)/Macrophage Activation Syndrome (MAS) [see Warnings and Precautions (5.4)]
- Hypersensitivity Reactions [see Warnings and Precautions (5.5)]
- Infections [see Warnings and Precautions (5.6)]
- Prolonged Cytopenias [see Warnings and Precautions (5.7)]
- Hypogammaglobulinemia [see Warnings and Precautions (5.8)]

6.1 Clinical Trials Experience

Because clinical trials are conducted under widely varying conditions, adverse reaction rates observed in the clinical trials of a drug cannot be directly compared to rates in the clinical trials of another drug and may not reflect the rates observed in clinical practice.

The safety data described in the WARNINGS and PRECAUTIONS section reflect exposure to ABECMA in 349 patients with relapsed or refractory multiple myeloma: one randomized, open-label study with 222 patients in Study 1 and one single-arm, open-label study with 127 patients in Study 2.

Study 1

The safety data described in this section reflect the exposure to ABECMA in Study 1, in which 222 patients with relapsed or refractory multiple myeloma received ABECMA across a dose range of 175 to 529 × 10^6 CAR-positive T cells (median dose: 445 × 10^6 CAR-positive T cells) [see Clinical Studies (14)]. Patients with a history of CNS disease or requiring ongoing treatment with chronic immunosuppression were excluded. The median age of the safety population was 63 years (range: 30 to 81 years); 43% were 65 years or older, and 63% were men. The Eastern Cooperative Oncology Group (ECOG) performance status at baseline was 0 in 47%, 1 in 51%, 2 in 1.4% and 3 in 0.5% of patients. Four (1.8%) patients treated with ABECMA had creatinine clearance <45 mL/min. For details about the study population, [see Clinical Studies (14)].

The most common (≥10%) Grade 3 or 4 nonlaboratory adverse reactions was febrile neutropenia (51%) and any infections (16%).

The most common nonlaboratory adverse reactions (incidence ≥20%) included CRS, pyrexia, any infection, febrile neutropenia, hypogammaglobulinemia, musculoskeletal pain, hypotension, infections–pathogen unspecified, fatigue, tachycardia, diarrhea, nausea, headache, encephalopathy, dyspnea and edema.

Serious adverse reactions occurred in 43% of patients. The most common nonlaboratory (≥5%) serious adverse reactions included infections–pathogen unspecified (10%), pneumonia (9%), viral infections (8%), encephalopathy (6%), pyrexia (6%) and sepsis (5%). Fatal adverse reactions occurred in 9%.

Table 3 summarizes the adverse reactions that occurred in at least 10% of patients treated with ABECMA. Table 4 describes the most common Grade 3 or 4 laboratory abnormalities.

Table 3: Adverse Reactions Observed in at Least 10% of Patients Treated in Study 1
 | ABECMA (N=222) |  | Standard Regimens (N=126)
 | Any Grade; (%) | Grade 3 or 4; (%) | Any Grade; (%) | Grade 3 or 4; (%)
Blood and lymphatic system disorders
Febrile neutropenia | 51 | 51 | 28 | 28
Coagulopathya | 14 | 2.7 | 4.8 | 0.8
Cardiac disorders
Tachycardia* | 32 | 0 | 21 | 0
Gastrointestinal disorders
Diarrhea* | 31 | 2.3 | 35 | 3.2
Nausea | 27 | 0.9 | 48 | 0
Constipation | 17 | 0 | 15 | 0
Vomiting* | 14 | 0 | 17 | 0
Abdominal pain* | 10 | 0.5 | 14 | 0
General disorders and administration site conditions
Pyrexia | 91 | 9 | 53 | 6
Fatigue* | 33 | 1.4 | 48 | 4
Edema* | 20 | 0.5 | 28 | 2.4
Chills | 19 | 0.5 | 13 | 0
Immune system disorders
Cytokine release syndrome | 91 | 4.1 | 40 | 0.8
Hypogammaglobulinemia | 48 | 0.9 | 25 | 0
Infections and infestations
Any infection | 56 | 16 | 64 | 18
Infections–pathogen unspecified* | 35 | 9 | 40 | 11
Upper respiratory tract infection* | 19 | 1.8 | 17 | 0.8
Infections–viral* | 18 | 5 | 28 | 6
Infections–bacterial* | 15 | 4.5 | 19 | 8
Pneumonia* | 13 | 8 | 13 | 11
Metabolism and nutrition disorders
Decreased appetite | 17 | 1.8 | 21 | 0
Musculoskeletal and connective tissue disorders
Musculoskeletal pain* | 36 | 1.8 | 49 | 8
Nervous system disorders
Headache* | 24 | 0 | 29 | 1.6
Encephalopathyb | 22 | 3.6 | 21 | 4.8
Dizziness* | 14 | 1.8 | 18 | 3.2
Neuropathyc | 10 | 0 | 21 | 0.8
Psychiatric disorders
Sleep disorder* | 11 | 0 | 22 | 2.4
Renal and urinary disorders
Renal failure* | 13 | 5 | 15 | 4
Respiratory, thoracic, and mediastinal disorders
Dyspnea* | 21 | 1.8 | 31 | 2.4
Cough* | 14 | 0 | 21 | 0
Hypoxia* | 18 | 6 | 8 | 1.6
Vascular disorders
Hypotension* | 36 | 2.3 | 19 | 1.6
Hypertension | 14 | 7 | 21 | 11
Skin disorders
Rash* | 10 | 0 | 19 | 0.8
CAR=chimeric antigen receptor.
* Represents multiple related terms.
a Coagulopathy includes activated partial thromboplastin time prolonged, blood fibrinogen decreased, coagulopathy, disseminated intravascular coagulation, hypofibrinogenemia, international normalized ratio increased, prothrombin time prolonged.
b Encephalopathy includes amnesia, cognitive disorder, confusional state, depressed level of consciousness, disturbance in attention, dysgraphia, encephalopathy, Immune effector cell-associated neurotoxicity syndrome incoherent, lethargy, memory impairment, mental status changes, metabolic encephalopathy, somnolence, stupor, toxic encephalopathy.
c Neuropathy includes carpal tunnel syndrome, dysesthesia, hyperesthesia, hypoesthesia, hypoesthesia oral, mononeuropathy, neuralgia, neuritis, neuropathy peripheral, paresthesia, paresthesia oral, peripheral motor neuropathy, peripheral sensorimotor neuropathy, peripheral sensory neuropathy, peroneal nerve palsy, radicular pain, radiculopathy, sacral radiculopathy, sciatica, sensory loss, toxic neuropathy.

Other clinically important adverse reactions that occurred in less than 10% of patients treated with ABECMA include the following:

- Cardiac disorders: cardiac arrhythmia (7%)
- Gastrointestinal disorders: gastrointestinal hemorrhage (0.5%)
- Immune system disorders: hemophagocytic lymphohistiocytosis (2.3%)
- Infections and infestations: infections-fungal (5%), sepsis (6%)
- Musculoskeletal and connective tissue disorders: motor dysfunction (9%)
- Nervous system disorders: tremor (4.1%), aphasia (3.2%), ataxia (2.3%), seizure (0.5%)
- Psychiatric disorders: anxiety (4.1%), delirium (7%)
- Respiratory, thoracic, and mediastinal disorders: pulmonary edema (1.4%)
- Vascular disorders: thrombosis (3.2%)

Laboratory Abnormalities

Table 4 presents the most common Grade 3 or 4 laboratory abnormalities, based on laboratory data, occurring in at least 10% of patients.

Table 4: Grade 3 or 4a Laboratory Abnormalities Worsening from Baseline in at Least 10% of Patients Treated in Study 1
Laboratory Abnormality | ABECMA; N=222; (%) | Standard Regimens; N=126; (%)
Laboratory Abnormality | Grade 3 or 4 (%) | Grade 3 or 4 (%)
Lymphocyte decreased | 98 | 78
Leukocyte decreased | 96 | 64
Neutrophil decreased | 96 | 72
Platelet decreased | 59 | 46
Hemoglobin decreased | 52 | 45
Phosphate decreased | 45 | 30
Triglyceride increased | 21 | 10
Alanine aminotransferase increased | 13 | 8
Sodium decreased | 11 | 7
Gamma-glutamyltransferase increased | 10 | 6
CAR=chimeric antigen receptor; CTCAE=Common Terminology Criteria for Adverse Events; NCI=National Cancer Institute.
a Laboratory tests were graded according to NCI CTCAE Version 4.03.

Other clinically important Grade 3 or 4 laboratory abnormalities (based on laboratory data) that occurred in less than 10% of patients treated with ABECMA include the following: aspartate aminotransferase increased, potassium decreased, albumin decreased, alkaline phosphatase increased, calcium decreased, glucose increased, activated partial thromboplastin time increased (seconds), fibrinogen decreased, bilirubin increased and hypomagnesemia.

Study 2

The safety data described in this section reflect the exposure to ABECMA in Study 2, in which 127 patients with relapsed/refractory multiple myeloma received ABECMA across a dose range of 150 to 518 × 10^6 CAR-positive T cells [see Clinical Studies (14)]. Patients with a history of CNS disease (such as seizure or cerebrovascular ischemia) or requiring ongoing treatment with chronic immunosuppression were excluded. The median duration of follow-up was 11.4 months. The median age of the study population was 61 years (range: 33 to 78 years); 35% were 65 years or older, and 60% were men. The Eastern Cooperative Oncology Group (ECOG) performance status at baseline was 0 in 45%, 1 in 53%, and 2 in 2% of patients. Seven percent of the patients treated with ABECMA had creatinine clearance <45 mL/min. For details about the study population, [see Clinical Studies (14)].

The most common (≥10%) Grade 3 or 4 nonlaboratory adverse reactions were febrile neutropenia (16%) and infections–pathogen unspecified (15%).

The most common nonlaboratory adverse reactions (incidence ≥20%) included CRS, infections–pathogen unspecified, fatigue, musculoskeletal pain, hypogammaglobulinemia, diarrhea, upper respiratory tract infection, nausea, viral infections, encephalopathy, edema, pyrexia, cough, headache, and decreased appetite.

Serious adverse reactions occurred in 67% of patients. The most common nonlaboratory (≥5%) serious adverse reactions included CRS (18%), general physical health deterioration (10%), pneumonia (12%), infections–pathogen unspecified (19%), viral infections (9%), sepsis (7%), and febrile neutropenia (6%). Fatal adverse reactions occurred in 6%.

Table 5 summarizes the adverse reactions that occurred in at least 10% of patients treated with ABECMA. Table 6 describes the most common Grade 3 or 4 laboratory abnormalities.

Table 5: Adverse Reactions Observed in at Least 10% of Patients Treated with ABECMA in Study 2
System Organ Class Preferred Term | Target Dose of ABECMA (CAR-Positive T Cells)
System Organ Class Preferred Term | Any Grade | Grade 3 or Higher
System Organ Class Preferred Term | [150 to 450 × 10^6] (N=127) % | [150 to 450 × 10^6] (N=127) %
Blood and lymphatic system disorders
Febrile neutropenia | 16 | 16
Cardiac disorders
Tachycardia* | 19 | 0
Gastrointestinal disorders
Diarrhea | 35 | 1.6
Nausea | 29 | 0
Constipation | 16 | 0
Vomiting | 15 | 0
Oral pain* | 12 | 0
General disorders and administration site conditions
Fatigue* | 45 | 3.1
Pyrexia | 25 | 1.6
General physical health deterioration | 11 | 10
Edema* | 25 | 0
Chills | 11 | 0
Immune system disorders
Cytokine release syndrome | 85 | 9
Hypogammaglobulinemia* | 41 | 0.8
Infections and infestations*
Infections–Pathogen unspecified | 51 | 15
Viral infections | 27 | 9
Bacterial infections | 15 | 3.9
Pneumonia* | 17 | 9
Upper respiratory tract infection* | 34 | 1.6
Investigations
Weight decreased | 13 | 1.6
Metabolism and nutrition disorders
Decreased appetite* | 22 | 0.8
Musculoskeletal and connective tissue disorders
Musculoskeletal pain* | 45 | 3.1
Motor dysfunction* | 11 | 0
Nervous system disorders
Encephalopathya | 26 | 6
Headache* | 23 | 0
Dizziness* | 17 | 0.8
Neuropathy peripheralb | 17 | 0.8
Tremor* | 10 | 0
Psychiatric disorders
Insomnia* | 13 | 0
Anxiety* | 12 | 0.8
Renal and urinary disorders
Renal failure* | 10 | 2.4
Respiratory, thoracic, and mediastinal disorders
Cough* | 23 | 0
Dyspnea* | 13 | 2.4
Skin and subcutaneous tissue disorder
Rash* | 14 | 0.8
Xerosis* | 11 | 0
Vascular disorders
Hypotension* | 17 | 0
Hypertension | 11 | 3.1
CAR=chimeric antigen receptor.
* Represents multiple related terms.
a Encephalopathy includes amnesia, bradyphrenia, cognitive disorder, confusional state, depressed level of consciousness, disturbance in attention, dyscalculia, dysgraphia, encephalopathy, lethargy, memory impairment, mental status changes, metabolic encephalopathy, somnolence, toxic encephalopathy.
b Neuropathy peripheral includes carpal tunnel syndrome, hypoesthesia, hypoesthesia oral, neuralgia, neuropathy peripheral, paresthesia, peripheral sensorimotor neuropathy, peripheral sensory neuropathy, sciatica.

Other clinically important adverse reactions that occurred in less than 10% of patients treated with ABECMA include the following:

- Blood and lymphatic system disorders: coagulopathy (9%)
- Cardiac disorders: atrial fibrillation (4.7%), cardiomyopathy (1.6%)
- Gastrointestinal disorders: gastrointestinal hemorrhage (3.1%)
- Immune system disorders: hemophagocytic lymphohistiocytosis (3.1%)
- Infections and infestations: fungal infections (8%), sepsis (9%)
- Nervous system disorders: aphasia (7%), ataxia (3.1%), paresis (2.4%), seizure (1.6%)
- Psychiatric disorders: delirium (6%)
- Respiratory, thoracic, and mediastinal disorders: hypoxia (2.4%), pulmonary edema (2.4%)
- Vascular disorders: thrombosis (3.1%)

Laboratory Abnormalities

Table 6 presents the most common Grade 3 or 4 laboratory abnormalities, based on laboratory data, occurring in at least 10% of patients.

Table 6: Grade 3 or 4a Laboratory Abnormalities Worsening from Baseline in at Least 10% of Patients Treated with ABECMA in Study 2
Laboratory Abnormality | Dose=[150 to 450 × 10^6 CAR-Positive T cells] (N=127) %
 | Grade 3 or 4 (%)
Neutrophil decreased | 96
Leukocyte decreased | 96
Lymphocyte decreased | 92
Platelet decreased | 63
Hemoglobin decreased | 63
Phosphate decreased | 45
Sodium decreased | 10
aPTT increased (seconds) | 10
aPTT=activated partial thromboplastin time; CAR=chimeric antigen receptor; CTCAE=Common Terminology Criteria for Adverse Events; NCI=National Cancer Institute
a NCI CTCAE=Common Terminology Criteria for Adverse Events version 4.03.

Other clinically important Grade 3 or 4 laboratory abnormalities (based on laboratory data) that occurred in less than 10% of patients treated with ABECMA include the following: alanine aminotransferase increased, aspartate aminotransferase increased, albumin decreased, alkaline phosphatase increased, glucose increased, potassium decreased, bilirubin increased, fibrinogen decreased, and calcium decreased.

6.2 Postmarketing Experience

Because adverse events to marketed products are reported voluntarily from a population of uncertain size, it is not always possible to reliably estimate their frequency or establish a causal relationship to product exposure.

The following adverse event has been identified during postmarketing use of ABECMA:

Nervous system disorders: Immune effector cell-associated neurotoxicity syndrome (ICANS).

The following adverse event has been identified during postmarketing use of BCMA- or CD19-directed genetically modified autologous T cell immunotherapies:

Neoplasms: T cell malignancies.

7 DRUG INTERACTIONS

Drug/Laboratory Test Interactions

HIV and the lentivirus used to make ABECMA have limited, short spans of identical genetic material (RNA). Therefore, some commercial HIV nucleic acid tests may yield false-positive results in patients who have received ABECMA.

8 USE IN SPECIFIC POPULATIONS

8.1 Pregnancy

Risk Summary

There are no available data with ABECMA use in pregnant women. No animal reproductive and developmental toxicity studies have been conducted with ABECMA to assess whether it can cause fetal harm when administered to a pregnant woman.

It is not known if ABECMA has the potential to be transferred to the fetus. Based on the mechanism of action, if the transduced cells cross the placenta, they may cause fetal toxicity, including plasma cell aplasia or hypogammaglobulinemia. Therefore, ABECMA is not recommended for women who are pregnant, and pregnancy after ABECMA infusion should be discussed with the treating physician. Assess immunoglobulin levels in newborns of mothers treated with ABECMA.

The estimated background risk of major birth defects and miscarriage for the indicated population is unknown. The estimated background risk in the U.S. general population of major birth defects is 2% to 4% and of miscarriage is 15% to 20% of clinically recognized pregnancies.

8.2 Lactation

Risk Summary

There is no information regarding the presence of ABECMA in human milk, the effect on the breastfed infant, and the effects on milk production. The developmental and health benefits of breastfeeding should be considered along with the mother's clinical need for ABECMA and any potential adverse effects on the breastfed infant from ABECMA or from the underlying maternal condition.

8.3 Females and Males of Reproductive Potential

Pregnancy Testing

Pregnancy status of sexually active females with reproductive potential should be verified via pregnancy testing prior to starting treatment with ABECMA.

Contraception

See the prescribing information for fludarabine and cyclophosphamide for information on the need for effective contraception in patients who receive the lymphodepleting chemotherapy.

There are insufficient exposure data to provide a recommendation concerning duration of contraception following treatment with ABECMA.

Infertility

There are no data on the effect of ABECMA on fertility.

8.4 Pediatric Use

The safety and efficacy of ABECMA in pediatric patients have not been established.

8.5 Geriatric Use

In the clinical trials of ABECMA, 141 (40%) of the 349 patients were 65 years of age or older and 16/349 (4.6%) patients were 75 years of age or older. In Study 2, all five cases of Grade 3 neurotoxicity occurred in patients ≥65 years of age (66 to 74 years). No clinically important differences in effectiveness of ABECMA were observed between these patients and patients younger than 65 years of age.

11 DESCRIPTION

ABECMA is a BCMA-directed genetically modified autologous T cell immunotherapy product consisting of a patient's own T cells that are harvested and genetically modified ex vivo through transduction with an anti-BCMA02 chimeric antigen receptor (CAR) lentiviral vector (LVV). Autologous T cells transduced with the anti-BCMA02 CAR LVV express the anti-BCMA CAR on the T cell surface. The CAR is comprised of a murine extracellular single-chain variable fragment (scFv) specific for recognizing B cell maturation antigen (BCMA) followed by a human CD8α hinge and transmembrane domain fused to the T cell cytoplasmic signaling domains of CD137 (4-1BB) and CD3ζ chain, in tandem. Binding of ABECMA to BCMA-expressing target cells leads to signaling initiated by CD3ζ and 4-1BB domains, and subsequent CAR-positive T cell activation. Antigen-specific activation of ABECMA results in CAR-positive T cell proliferation, cytokine secretion, and subsequent cytolytic killing of BCMA-expressing cells.

ABECMA is prepared from the patient's peripheral blood mononuclear cells (PBMCs), which are obtained via a standard leukapheresis procedure. The mononuclear cells are enriched for T cells, through activation with anti-CD3 and anti-CD28 antibodies in the presence of IL-2, which are then transduced with the replication-incompetent lentiviral vector containing the anti-BCMA CAR transgene. The transduced T cells are expanded in cell culture, washed, formulated into a suspension, and cryopreserved. The product must pass a sterility test before release for shipping as a frozen suspension in one or more patient-specific infusion bag(s). The product is thawed prior to infusion back into the patient [see Dosage and Administration (2.3) and How Supplied/Storage and Handling (16)].

The ABECMA formulation contains 50% Plasma-Lyte A and 50% CryoStor® CS10, resulting in a final DMSO concentration of 5%.

12 CLINICAL PHARMACOLOGY

12.1 Mechanism of Action

ABECMA is a chimeric antigen receptor (CAR)-positive T cell therapy targeting B-cell maturation antigen (BCMA), which is expressed on the surface of normal and malignant plasma cells. The CAR construct includes an anti-BCMA scFv-targeting domain for antigen specificity, a transmembrane domain, a CD3-zeta T cell activation domain, and a 4-1BB costimulatory domain. Antigen-specific activation of ABECMA results in CAR-positive T cell proliferation, cytokine secretion, and subsequent cytolytic killing of BCMA-expressing cells.

12.2 Pharmacodynamics

Following ABECMA infusion, pharmacodynamic responses of CAR activation and anti-tumor efficacy were evaluated. Peak elevation of plasma cytokines, chemokines, and soluble immune mediators occurred within 14 days of ABECMA infusion and returned to baseline levels within one month.

Rapid decreases in tumor markers associated with clinical response, including serum levels of soluble BCMA, and bone marrow CD138+ cells, as well as minimal residual disease (MRD) negative responses, were observed within the first month following ABECMA infusion.

12.3 Pharmacokinetics

Following ABECMA infusion, the CAR-positive T cells proliferate and undergo rapid multi-log expansion followed by a bi-exponential decline. The median time of maximal expansion in peripheral blood (Tmax) occurred 11 days after infusion.

ABECMA can persist in peripheral blood for up to 1 year post-infusion. A summary of Tmax, AUC0-28days, and Cmax from Study 1 and Study 2 is provided in Table 7.

Table 7: Pharmacokinetic Parameters of ABECMA in Patients with Relapsed/Refractory Multiple Myeloma
Pharmacokinetic Parameter | Summary Statistic | Study 1; Total [300 to 510 × 10^6]; CAR-Positive T Cells; (Quantified by ddPCR)a | Study 2; Total; [300 to 460 × 10^6]; CAR-Positive T Cells; (Quantified by qPCR)b
Tmax (days) | Median (Range) | 11 (4-31) N=207 | 11 (7-28); N=99
Cmax (copies/mcg) | Geometric mean (geometric CV%) | 117,557 (215); N=207 | 256,333 (165); N=99
AUC0-28days (days* copies/mcg) | Geometric mean (geometric CV%) | 1,098,862 (228) N=205 | 3,088,455 (190); N=98
AUC0-28days=area under the curve of the transgene level from time of dose to 28 days post-infusion; Cmax=the maximum transgene level; ddPCR=droplet digital polymerase chain reaction; qPCR=quantitative polymerase chain reaction; PK=pharmacokinetics; Tmax=time of maximum observed transgene level.
a The PK parameters of Study 1 were determined by time course of transgene copies per microgram of DNA extracted from whole blood as quantified by droplet digital PCR (ddPCR).
b The PK parameters of Study 2 were determined by time course of transgene copies per microgram of DNA extracted from CD3+ sorted cells as quantified by quantitative polymerase chain reaction (qPCR).
Note: The PK parameters should not be directly compared between Study 1 and Study 2 due to different primary PK assays used in these two studies.

ABECMA transgene levels were positively associated with objective tumor response (partial response or better). Among patients who received ABECMA in Study 1, the median Cmax levels in responders (N=172) were approximately 6.5-fold higher compared to the corresponding levels in non-responders (N=35). Median AUC0-28days in responders (N=172) was approximately 6.1-fold higher than non-responders (N=33). Among patients who received ABECMA in Study 2, the median Cmax levels in responders (N=72) were approximately 4.6-fold higher than the corresponding levels in non-responders (N=27). Median AUC0-28days in responders (N=72) was approximately 5.6-fold higher than non-responders (N=26).

Tocilizumab or Siltuximab and Corticosteroid Use

Some patients required tocilizumab or siltuximab and/or corticosteroid for the management of CRS. ABECMA can continue to expand and persist following tocilizumab or siltuximab or corticosteroid administration [see Warnings and Precautions (5.2)].

In Study 2, patients with CRS treated with tocilizumab had higher ABECMA cellular expansion levels, as measured by 1.3‑fold and 1.6-fold higher median Cmax (N=67) and AUC0‑28days (N=66), respectively, compared to patients who did not receive tocilizumab (N=59 for Cmax and N=58 for AUC0‑28days).

Patients with CRS treated with corticosteroids had higher ABECMA cellular expansion levels, as measured by 1.7-fold and 2.2-fold higher median Cmax (N=18) and AUC0‑28days (N=18), respectively, compared to patients who did not receive corticosteroids (N=108 for Cmax and N=106 for AUC0‑28days).

Similar trend was observed in Study 1.

Specific Populations

Geriatric

Age (range: 30 to 81 years) had no significant impact on expansion parameters [see Use in Special Populations (8.5)].

Pediatric

The pharmacokinetics of ABECMA in patients less than 18 years of age have not been evaluated.

Patients with Hepatic/Renal Impairment

Hepatic and renal impairment studies of ABECMA were not conducted.

Patients with Other Intrinsic Factors

Gender, race, and ethnicity had no significant impact on ABECMA expansion parameters. Patients with lower body weight had higher expansion. Due to high variability in pharmacokinetic cellular expansion, the overall effect of weight on the pharmacokinetics of ABECMA is considered to be not clinically relevant.

12.6 Immunogenicity

The observed incidence of anti-drug antibodies is highly dependent on the sensitivity and specificity of the assay. Differences in assay methods preclude meaningful comparisons of the incidence of anti-drug antibodies in the studies described below with the incidence of anti-drug antibodies in other studies, including those of ABECMA or of other similar products.

In Study 1 and Study 2, humoral immunogenicity of ABECMA was measured by determination of anti-CAR antibody in serum pre- and post-administration. In the clinical studies, 2.6% of patients (9/349) tested positive for pre-infusion anti-CAR antibodies and treatment-induced anti-CAR antibodies were detected in 53% (186/349) of the patients. There is no identified clinically significant impact of pre-existing or post-infusion anti-CAR antibodies on the cellular expansion, safety, or effectiveness of ABECMA.

13 NONCLINICAL TOXICOLOGY

13.1 Carcinogenesis, Mutagenesis, Impairment of Fertility

Genotoxicity assays and carcinogenicity studies in rodents were not performed for ABECMA.

In vitro expansion studies with CAR-positive T cells (ABECMA) from five patients and two healthy donor drug product lots showed no evidence for transformation and/or immortalization of T cells. A genomic insertion site analysis of the lentiviral vector was performed on ABECMA samples from twenty (20) individual patient donors. There was no evidence for preferential integration near genes of concern or preferential outgrowth of cells harboring integration sites of concern.

No studies on the effects of ABECMA on fertility have been conducted.

14 CLINICAL STUDIES

The efficacy of ABECMA was evaluated in two studies, Study 1 (Study BB2121-MM-003; NCT03651128) and Study 2 (Study BB2121-MM-001; NCT03361748) as described below.

Study 1 (Relapsed/Refractory Multiple Myeloma After Two to Four Prior Lines of Therapy)

Study 1 was an open-label, multicenter, randomized, controlled study in adult patients with relapsed and refractory multiple myeloma who had received two to four prior antimyeloma therapies including an immunomodulatory agent, a proteasome inhibitor and daratumumab, and were refractory to the most recent prior antimyeloma regimen. The study included patients who achieved a response (minimal response or better) to at least 1 prior treatment regimen and had ECOG performance status of 0 or 1. The study excluded patients with serum creatinine clearance <45 mL/min, serum aspartate aminotransferase (AST) or alanine aminotransferase (ALT) >2.5 times upper limit of normal, and left ventricular ejection fraction (LVEF) <45%. Patients were also excluded if absolute neutrophil count <1000/µL and platelet count <75,000/μL in patients in whom <50% of bone marrow nucleated cells are plasma cells and platelet count <50,000/μL in patients in whom ≥50% of bone marrow nucleated cells are plasma cells.

In total, 386 patients were randomized 2:1 to receive either ABECMA (N=254) or standard regimens (N=132). The standard regimens consisted of daratumumab, pomalidomide, dexamethasone [DPd], daratumumab, bortezomib, dexamethasone [DVd], ixazomib, lenalidomide, dexamethasone [IRd], carfilzomib, dexamethasone [Kd], or elotuzumab, pomalidomide, dexamethasone [EPd]), selected by Investigator prior to randomization contingent upon the patient’s most recent antimyeloma treatment. Randomization was stratified by age, number of prior antimyeloma regimens, and presence of high-risk cytogenetics abnormalities.

Patients randomized to ABECMA were to receive lymphodepleting chemotherapy consisting of cyclophosphamide (300 mg/m^2 IV infusion daily for 3 days) and fludarabine (30 mg/m^2 IV infusion daily for 3 days) starting 5 days prior to the target infusion date of ABECMA. Up to 1 cycle of DPd, DVd, IRd, Kd or EPd bridging therapy, dependent on the patient’s most recent antimyeloma treatment regimen, was permitted for disease control between apheresis and until 14 days before the start of lymphodepleting chemotherapy.

Of the 254 patients randomized to receive ABECMA, 249 (98%) patients underwent leukapheresis:

- Five (2%) patients did not receive leukapheresis due to patient withdrawal (n=2), adverse event (n=1) or failure to meet lymphodepleting chemotherapy treatment criteria (n=2).
- Twenty-four (10%) patients did not receive ABECMA either due to death (n=4), adverse event (n=4), physician decision (n=7), failure to meet lymphodepleting chemotherapy treatment criteria (n=6) or inability to manufacture product (n=3).
- Three (1.2%) patients received CAR-positive T cells that did not meet product release specifications for ABECMA (non-conforming product; n=3).

The overall manufacturing failure rate for patients who underwent leukapheresis was 2.4% (6 out of 249 patients). Of these six patients, three received CAR positive T cells that did not meet product release specifications for ABECMA, and in three patients there was an inability to manufacture ABECMA.

Most patients (85%) treated with ABECMA received bridging therapy for control of their multiple myeloma during the manufacturing process. The median time from leukapheresis to product availability was 35 days (range: 24 to 102 days).

In overall study population, the median age was 63 years (range: 30 to 83 years), 61% were male, 65% were white, 9.3% were black and 3.1% were Asian. Most patients (80%) were Revised International Staging System (R-ISS) Stage I or II. High-risk cytogenetics [presence of t(4:14), (14:16), and 17p13 del] were present in 42% of patients. Twenty-four percent of patients had presence of extramedullary disease.

The median number of prior lines of therapy was 3 (range: 2 to 4). Thirty percent had received 2 prior lines, 37% had received 3 prior lines of therapy and 32% had received 4 prior lines of therapy. Ninety-five percent were refractory to an anti-CD38 monoclonal antibody. Sixty-six percent were triple class refractory (refractory to a PI, an IMiD and an anti-CD38 monoclonal antibody), and 5% were penta-drug-refractory (refractory to 2 PIs, 2 IMiD agents, and an anti-CD38 monoclonal antibody). Eighty-five percent of patients had received prior autologous stem cell transplantation.

The primary efficacy measure was progression free survival (PFS) as determined by Independent Review Committee (IRC) based on the International Myeloma Working Group (IMWG) Uniform Response Criteria^2 for Multiple Myeloma. Other efficacy measures included overall response rate (ORR) and overall survival (OS). Efficacy results are summarized in Table 8, and Kaplan-Meier curve for PFS is provided in Figure 2.

The estimated median duration of follow-up at the primary PFS analysis was 15.9 months (95% CI: 14.1, 18.0).

Table 8: Summary of Efficacy Results from Study 1 (Intent-to-Treat Population)
 | ABECMA Arm; (N=254) | Standard Regimens Arm; (N=132)
Progression Free Survival (PFS)
Number of events, n (%) | 149 (59) | 93 (70)
Median, months [95% CI]a | 13.3 [11.8, 16.1] | 4.4 [3.4, 5.9]
Hazard Ratio [95% CI]b | 0.49 [0.38, 0.64]
One-sided p-valuec | <0.0001
Overall Response Rate (ORR), n (%)
n (%) | 181 (71) | 55 (42)
95% CI (%)d | (66, 77) | (33, 50)
One-sided p-valuee | <0.0001
CR or better (sCR+CR) | 98 (39) | 7 (5)
sCR | 90 (35) | 6 (4.5)
CR | 8 (3.1) | 1 (0.8)
VGPR | 55 (22) | 13 (10)
PR | 28 (11) | 35 (27)
CI=confidence interval; CR=complete response; PR=partial response; sCR=stringent complete response; VGPR=very good partial response.
a Kaplan-Meier estimate.
b Based on stratified univariate Cox proportional hazards model.
c One-sided p-value is based on stratified log-rank test.
d Two-sided Wald confidence interval.
e One-sided p-value from Cochran-Mantel-Haenszel (CMH) test stratified by stratification factors.

Figure 2: Kaplan-Meier Plot of IRC-Assessed Progression Free Survival (Intent-to-Treat Analysis)

Data cutoff date: April 18, 2022

In the ABECMA arm, the median duration of response (DOR) was 14.8 months (95% CI: 12.0, 18.6) in patients with partial response (PR) or better. In those patients with CR or better, the median DOR was 20 months (95% CI: 15.8, 24.3).

A higher proportion of patients in the ABECMA arm compared to the standard regimen’s arm died within the first nine months of randomization as shown in Figure 3.

Figure 3: Kaplan-Meier Plot of Overall Survival (Intent-to-Treat Analysis) at Second Interim Analysis

Data cutoff date: April 28, 2023.

74% of the planned OS events have occurred.74 patients (56%) crossed over from the standard regimens arm to the ABECMA arm.

The OS curves cross at Month 15 of the study rendering the overall hazard ratio unreliable to estimate the treatment effect on OS.

Study 2 (Relapsed/Refractory Multiple Myeloma After Three or More Prior Lines of Therapy)

Study 2 was an open-label, single-arm, multicenter study in adult patients with relapsed and refractory multiple myeloma who had received at least 3 prior lines of antimyeloma therapy including an immunomodulatory agent, a proteasome inhibitor, and an anti-CD38 monoclonal antibody. The study included patients with ECOG performance status of 0 or 1. The study excluded patients with a creatinine clearance of less than or equal to 45 mL/minute, alanine aminotransferase >2.5 times upper limit of normal, and left ventricular ejection fraction <45%. Patients were also excluded if absolute neutrophil count <1000 cells/mm^3 and platelet count <50,000/mm^3. Patients had measurable disease by IMWG 2016 criteria at enrollment. Bridging therapy with alkylating agents, corticosteroids, immunomodulatory agents, proteasome inhibitors, and/or anti-CD38 monoclonal antibodies to which patients were previously exposed was permitted for disease control between apheresis and until 14 days before the start of lymphodepleting chemotherapy.

Lymphodepleting chemotherapy consisted of cyclophosphamide (300 mg/m^2 IV infusion daily for 3 days) and fludarabine (30 mg/m^2 IV infusion daily for 3 days) starting 5 days prior to the target infusion date of ABECMA. Fludarabine was dose reduced for renal insufficiency. Patients were hospitalized for 14 days after ABECMA infusion to monitor for potential CRS, HLH/MAS, and neurotoxicity.

Of the 135 patients who underwent leukapheresis for 300 × 10^6 and 450 × 10^6 CAR-positive T cell dose cohorts:

- 11 (8%) did not receive the CAR-positive T cells either due to death (n=2), adverse event (n=1), disease progression (n=1), consent withdrawal (n=3), physician decision (n=3), or inability to manufacture product [manufacturing failure (n=1)]. Two patients died after receiving lymphodepletion and prior to receiving ABECMA. Deaths were from septic shock and general physical health deterioration.
- 24 (18%) either received ABECMA outside of the 300 to 460 x 10^6 CAR-positive T cells dose range (n=23) or received CAR-positive T cells that did not meet product release specifications for ABECMA (non-conforming product; n=1).
- The efficacy evaluable population consists of the 100 patients (74%) who received ABECMA in the dose range of 300 to 460 x 10^6 CAR-positive T cells.

The overall manufacturing failure rate for patients who underwent leukapheresis for the 300 × 10^6 and 450 × 10^6 CAR-positive T cell dose cohorts was 1.5% (2 out of 135 patients). Of these two patients, one received CAR‑positive T cells that did not meet product release specifications for ABECMA, and in one patient there was an inability to manufacture ABECMA.

Of the 100 patients in the efficacy evaluable population, the median age was 62 years (range: 33 to 78 years), 60% were male, 78% were white, 6% were black, and 2% were Asian. Most patients (78%) were International Staging System (ISS) Stage I or II. High‑risk cytogenetics (presence of t(4:14), t(14:16), and 17p13 del) were present in 37% of patients. Thirty-six percent of the patients had presence of extramedullary disease.

The median number of prior lines of therapy was 6 (range: 3 to 16), and 88% of the patients received 4 or more prior lines of therapy. Ninety-five percent of the patients were refractory to an anti-CD38 monoclonal antibody. Eighty-five percent were triple class refractory (refractory to a proteasome inhibitor [PI], an immunomodulatory drug [IMiD], and an anti-CD38 monoclonal antibody), and 26% were penta-refractory (refractory to 2 PIs, 2 IMiD agents, and an anti-CD38 monoclonal antibody). Ninety-two percent had received prior autologous stem cell transplantation.

Most patients (87%) treated with ABECMA received bridging therapy for control of their multiple myeloma during the manufacturing process. The median time from leukapheresis to product availability was 33 days (range: 26 to 49 days).

Efficacy was established on the basis of overall response rate (ORR), complete response (CR) rate, and duration of response (DOR), as assessed by the Independent Response committee (IRC) based on the International Myeloma Working Group (IMWG) Uniform Response Criteria for Multiple Myeloma.

Efficacy results for the dose range of 300 to 460 × 10^6 CAR-positive T cells are shown in Table 9 and Table 10, and the DOR results are shown in Table 11. The median time to first response was 30 days (range: 15 to 88 days).

Table 9: Summary of Efficacy Based on Independent Response Committee Review According to IMWG Criteria (Study 2)
 | ABECMA-Treated Population (300 to 460 × 10^6 CAR-Positive T Cells); N=100
Overall Response Rate; (sCRa+VGPR+PR), n (%); 95% CIb (%) | 72 (72); 62, 81
sCRa, n (%); 95% CIb (%) | 28 (28); 19, 38
VGPR, n (%); 95% CIb (%) | 25 (25); 17, 35
PR, n (%); 95% CIb (%) | 19 (19); 12, 28
CAR=chimeric antigen receptor; CI=confidence interval; CR=complete response; MRD=Minimal Residual Disease; IMWG=International Myeloma Working Group; PR=partial response; sCR=stringent complete response; VGPR=very good partial response.
a All complete responses were stringent CRs.
b Clopper-Pearson exact CI.

Table 10: MRD Negativity Rate in Study 2
MRDa-negativity rateb in all treated patients (n=100); 95% CIc (%) | 21 (21); 13, 30
MRDa-negativity rateb in patients achieving CR or sCR status (%) (n=28); 95% CIc | 21 (75); 55, 89
a Based on a threshold of 10^-5 using ClonoSEQ, a next-generation sequencing assay (NGS).
b MRD negativity was defined as the proportion of patients with CR or stringent CR who are MRD negative at any timepoint within three months prior to achieving CR or stringent CR until the time of progression or death.
c Clopper-Pearson exact CI.

Table 11: Duration of Response in Study 2
 | ABECMA-Treated Population (300 to 460 × 10^6 CAR-Positive T Cells); N=100
Duration of Responsea,b (PR or Better); n; Median (months); 95% CI | 72; 11.0; 10.3, 11.4
Duration of Responseb for sCR; n; Median (months); 95% CI | 28; 19.0; 11.4, NE
Median follow-up for duration of response (DOR) | 10.7 months
CAR=chimeric antigen receptor; CI=confidence interval; CR=complete response; PR=partial response; sCR=stringent complete response; VGPR=very good partial response; NE=not estimable.
a Response is defined as achieving sCR, CR, VGPR, or PR according to IMWG criteria.
b Median and 95% CI are based on Kaplan-Meier estimation.

Response durations were longer in patients who achieved a stringent CR as compared to patients with a PR or VGPR (Table 11). Of the 28 patients who achieved a stringent CR, it is estimated that 65% (95% CI: 42%, 81%) had a remission lasting at least 12 months.

The median duration of response for VGPR patients (n=25) was 11.1 months (95% CI: 8.7, 11.3).

The median duration of response for PR patients (n=19) was 4.0 months (95% CI: 2.7, 7.2).

Within the recommended dose of 300 to 460 × 10^6 CAR-positive T cells, a dose-response relationship was observed with higher ORR and sCR rate in patients who received 440 to 460 × 10^6 compared to 300 to 340 × 10^6 CAR-positive T cells. Overall response rate of 79% (95% CI: 65%, 90%) and sCR rate of 31% (95% CI: 19%, 46%) was observed with 440 to 460 × 10^6 CAR-positive T cells. Overall response rate of 65% (95% CI: 51%, 78%) with sCR rate of 25% (95% CI: 14%, 39%) was observed in 300 to 340 × 10^6 CAR-positive T cells.

One hundred and thirty-five patients underwent leukapheresis. Fifteen out of the 23 patients who received treatment outside of the recommended dose range of 300 to 460 x 10^6 CAR-positive T cells experienced a response in addition to the responses noted in Table 9. The IRC assessed overall response in the leukapheresis population (n=135) was 64% (95% CI: 56%, 72%) with stringent CR rate of 24% (95% CI: 17%, 32%), VGPR rate of 21% (95% CI: 14%, 29%), and PR rate of 20% (95% CI: 14%, 28%).

15 REFERENCES

1. Lee DW, Gardner R, Porter DL, et al. Current concepts in the diagnosis and management of cytokine release syndrome. Blood 2014; 124(2): 188-95. Errata in Blood: 2015;126(8):1048. and 2016;128(11):1533.
2. Kumar S, Paiva B, Anderson KC, et al. International Myeloma Working Group consensus criteria for response and minimal residual disease assessment in multiple myeloma. Lancet Oncol 2016; 17(8): e328-46.

16 HOW SUPPLIED/STORAGE AND HANDLING

ABECMA is supplied in one or more infusion bag(s) (see below) containing a frozen suspension of genetically modified autologous T cells in 5% DMSO.

Each infusion bag of ABECMA is overwrapped with a transparent plastic sleeve that is folded to the back of the infusion bag and individually packed in a metal cassette. ABECMA is stored in the vapor phase of liquid nitrogen and supplied in a liquid nitrogen dry vapor shipper. An RFI Certificate is affixed inside the shipper.

- 50 mL infusion bag and metal cassette (NDC 59572-515-01)
- 250 mL infusion bag and metal cassette (NDC 59572-515-02)
- 500 mL infusion bag and metal cassette (NDC 59572-515-03)

Match the identity of the patient with the patient identifiers on the cassette(s) and infusion bag(s) upon receipt.

STORAGE AND HANDLING

Store ABECMA frozen in the vapor phase of liquid nitrogen (less than or equal to minus 130°C).

Thaw ABECMA prior to infusion [see Dosage and Administration (2.2)].

17 PATIENT COUNSELING INFORMATION

Advise the patient to read the FDA-approved patient labeling (Medication Guide).

Advise patients that the risk of manufacturing failure is 2.1% [8/384 in the clinical studies]. In case of a manufacturing failure, a second manufacturing of ABECMA may be attempted. In addition, while the patient awaits the product, additional anticancer treatment (not the lymphodepletion) may be necessary and may increase the risk of adverse events during the pre-infusion period, which could delay or prevent the administration of ABECMA.

Inform patients of the risk of early death: In a clinical study, a higher proportion of patients experienced death within the first nine months from randomization in the ABECMA arm compared to the standard regimens arm. This higher rate of early death was mainly observed before receiving ABECMA with the main reason being progression of multiple myeloma. There was also an increase in the rate of death from adverse events after ABECMA.

Advise patients to seek immediate attention for any of the following:

- Cytokine Release Syndrome (CRS): Signs or symptoms associated with CRS, including fever, hypotension, tachycardia, chills, hypoxia, headache, and fatigue [see Dosage and Administration (2.3), Warnings and Precautions (5.2), and Adverse Reactions (6.1)].
- Neurologic Toxicities: Signs or symptoms associated with neurologic events, including encephalopathy, confusion, seizures, tremor, aphasia, delirium, and somnolence [see Dosage and Administration (2.3), Warnings and Precautions (5.3), and Adverse Reactions (6.1)].
- Infections: Signs or symptoms associated with infection [see Warnings and Precautions (5.6) and Adverse Reactions (6.1)].
- Prolonged Cytopenias: Signs or symptoms associated with bone marrow suppression, including neutropenia, anemia, thrombocytopenia, or febrile neutropenia [see Warnings and Precautions (5.7) and Adverse Reactions (6.1)].
- Secondary malignancies: Secondary malignancies, including T cell malignancies, have occurred [see Boxed Warning, Warnings and Precautions (5.9), Adverse Reactions (6.3)].

Advise patients for the need to:

- Contact Bristol-Myers Squibb at 1-888-805-4555 if they are diagnosed with a secondary malignancy [see Warnings and Precautions (5.9)].
- Have periodic monitoring of blood counts before and after ABECMA infusion [see Warnings and Precautions (5.7)].
- Avoid driving for at least one week.

Manufactured by: Celgene Corporation, a Bristol-Myers Squibb Company
  556 Morris Avenue
  Summit, NJ 07901
U.S. License No. 2252

Marketed by: Celgene Corporation, a Bristol-Myers Squibb Company (Summit, NJ 07901).

ABECMA® is a trademark of Celgene Corporation, a Bristol-Myers Squibb Company.
Pat. https://www.bms.com/patient-and-caregivers/our-medicines.html
ABEPI.009/MG.004

MEDICATION GUIDE
ABECMA® (uh-BEK-muh)
(idecabtagene vicleucel)

Read this Medication Guide before you start your ABECMA treatment. The more you know about your treatment, the more active you can be in your care. Talk with your healthcare provider if you have questions about your health condition or treatment. Reading this Medication Guide does not take the place of talking with your healthcare provider about your treatment.

What is the most important information I should know about ABECMA?
ABECMA may cause side effects that are life-threatening and can lead to death. Call your healthcare provider or get emergency help right away if you get any of the following:

- difficulty breathing
- fever (100.4°F/38°C or higher)
- chills/shivering
- confusion
- dizziness or lightheadedness
- shaking or twitching (tremor)
- fast or irregular heartbeat
- severe fatigue
- severe nausea, vomiting, diarrhea

It is important that you tell your healthcare providers that you have received ABECMA and to show them your ABECMA Patient Wallet Card. Your healthcare provider may give you other medicines to treat your side effects.

What is ABECMA?
ABECMA is for the treatment of multiple myeloma in patients who have received at least two kinds of treatment regimens that have not worked or have stopped working. ABECMA is a medicine made from your own white blood cells; the cells are genetically modified to recognize and attack your multiple myeloma cells.

How will I receive ABECMA?
ABECMA is made from your own white blood cells, so your blood will be collected by a process called "leukapheresis" (LOO-kuh-feh-REE-sis).
Your blood cells will be sent to a manufacturing center to make your ABECMA. Based on clinical trial experience, it takes about four weeks from the time your cells are received at the manufacturing site and are available to be shipped back to your healthcare provider, but the time may vary.
Before you get ABECMA, your healthcare provider will give you chemotherapy for three days to prepare your body.
When your ABECMA is ready, your healthcare provider will give ABECMA to you through a catheter (tube) placed into your vein (intravenous infusion). Your dose of ABECMA may be given in one or more infusion bags. The infusion usually takes up to 30 minutes for each infusion bag.
You will be monitored daily for at least seven days after the infusion.
You should plan to stay close to a healthcare facility for at least one week after getting ABECMA. Your healthcare provider will check to see that your treatment is working and help you with any side effects that may occur.

What should I avoid after receiving ABECMA?

- Avoid driving for at least one week after you get ABECMA.
- Do not donate blood, organs, tissues, or cells for transplantation.

What are the possible or reasonably likely side effects of ABECMA?
The most common side effects of ABECMA are:

- fatigue
- fever (100.4°F/38°C or higher)
- chills/shivering
- severe nausea or diarrhea
- decreased appetite
- headache
- dizziness/lightheadedness
- confusion
- difficulty speaking or slurred speech
- cough
- difficulty breathing
- fast or irregular heartbeat

In a study comparing ABECMA to standard regimen, a higher proportion of patients experienced death within the first nine months from randomization in the ABECMA arm compared to the standard regimens arm. This higher rate of early death was mainly observed before receiving ABECMA with the main reason being progression of multiple myeloma. There was also an increase in the rate of death from adverse events after ABECMA.

ABECMA can cause a very common side effect called cytokine release syndrome or CRS, which can be severe or fatal. Symptoms of CRS include fever, difficulty breathing, dizziness or light-headedness, nausea, headache, fast heartbeat, low blood pressure, or fatigue. Tell your healthcare provider right away if you develop fever or any of these other symptoms after receiving ABECMA.

ABECMA can increase the risk of life-threatening infections that may lead to death. Tell your healthcare provider right away if you develop fever, chills, or any signs or symptoms of an infection.

ABECMA can lower one or more types of your blood cells (red blood cells, white blood cells, or platelets), which may make you feel weak or tired or increase your risk of severe infection or bleeding. After treatment, your healthcare provider will test your blood to check for this. Tell your healthcare provider right away if you get a fever, are feeling tired, or have bruising or bleeding.

ABECMA may increase your risk of getting cancers including certain types of blood cancers. Your healthcare provider should monitor you for this.

Having ABECMA in your blood may cause a false-positive human immunodeficiency virus (HIV) test result by some commercial tests.

These are not all the possible side effects of ABECMA. Call your doctor for medical advice about side effects. You may report side effects to FDA at 1-800-FDA-1088.

General information about the safe and effective use of ABECMA
Medicines are sometimes prescribed for purposes other than those listed in a Medication Guide. If you would like more information about ABECMA, talk with your healthcare provider. You can ask your healthcare provider for information about ABECMA that is written for health professionals.
For more information, go to ABECMA.com or call 1-888-805-4555.
Manufactured by: Celgene Corporation, a Bristol-Myers Squibb Company, 556 Morris Avenue, Summit, NJ 07901.
Marketed by: Celgene Corporation, a Bristol-Myers Squibb Company (Summit, NJ 07901).
ABECMA® is a trademark of Celgene Corporation, a Bristol-Myers Squibb Company.
ABEMG004 11/2025

This Medication Guide has been approved by the U.S. Food and Drug Administration.
Revised: November 2025

PRINCIPAL DISPLAY PANEL - 30 mL Bag Label

idecabtagene vicleucel
Abecma™

NDC 59572-515-01
Genetically modified autologous T cells
FOR AUTOLOGOUS AND INTRAVENOUS USE ONLY

Suspension for IV Infusion
Rx Only

Acceptable Volume 10mL - 30mL per bag

Dosage: See prescribing information and
Release for Infusion Certificate (inside shipper).

Contains: 300 to 510 x 10^6 anti-BCMA02
CAR-positive T cells in cryopreservative
solution containing 5% DMSO USP.
Dose may be suspended in 1 or more
infusion bag(s).

Do not use a leukodepleting filter
or irradiate.

Not evaluated for infectious substances.
Preservative free.

Store in vapor phase of liquid nitrogen
(≤ -130°C).

Mfd by: Celgene Corporation,
a Bristol-Myers Squibb Company
Summit, NJ 07901 USA
Phone: 1-888-805-4555
US License No. 2252

First: FIRST NAME
Last: LAST NAME
Date of birth: DD-MMM-YYYY
DIN/Aph ID: W0000 00 000000
JOIN: XXXX-XXXXX
LOT: XXXX-XXXXXY
EXP: DD-MMM-YYYY

Bag ID: XX

XXXX-XXXXXY-XX

304492

PRINCIPAL DISPLAY PANEL - 30 mL Cassette Label

idecabtagene vicleucel
Abecma™

NDC 59572-515-01
Genetically modified autologous T cells
FOR AUTOLOGOUS AND INTRAVENOUS USE ONLY

Suspension for IV Infusion
Rx Only

Acceptable Volume 10mL - 30mL per bag

Dosage: See prescribing information and Release for
Infusion Certificate (inside shipper).

Contains: 300 to 510 x 10^6 anti-BCMA02 CAR-positive T cells
in cryopreservative solution containing 5% DMSO USP.
Dose may be suspended in 1 or more infusion bag(s).

Do not use a leukodepleting filter or irradiate.

Not evaluated for infectious substances. Preservative free.

Store in vapor phase of liquid nitrogen (≤ -130°C).

Mfd by: Celgene Corporation, a Bristol-Myers Squibb Company
Summit, NJ 07901 USA
Phone: 1-888-805-4555
US License No. 2252

First: FIRST NAME
Last: LAST NAME
Date of birth: DD-MMM-YYYY
DIN/Aph ID: W0000 00 000000
JOIN: XXXX-XXXXX
LOT: XXXX-XXXXXY
EXP: DD-MMM-YYYY

Bag ID: XX

XXXX-XXXXXY-XX

304493

PRINCIPAL DISPLAY PANEL - 70 mL Bag Label

idecabtagene vicleucel
Abecma™

NDC 59572-515-02
Genetically modified autologous T cells
FOR AUTOLOGOUS AND INTRAVENOUS USE ONLY

Suspension for IV Infusion
Rx Only

Acceptable Volume 30mL - 70mL per bag

Dosage: See prescribing information and
Release for Infusion Certificate (inside shipper).

Contains: 300 to 510 x 10^6 anti-BCMA02
CAR-positive T cells in cryopreservative
solution containing 5% DMSO USP.
Dose may be suspended in 1 or more
infusion bag(s).

Do not use a leukodepleting filter
or irradiate.

Not evaluated for infectious substances.
Preservative free.

Store in vapor phase of liquid nitrogen
(≤ -130°C).

Mfd by: Celgene Corporation,
a Bristol-Myers Squibb Company
Summit, NJ 07901 USA
Phone: 1-888-805-4555
US License No. 2252

First: FIRST NAME
Last: LAST NAME
Date of birth: DD-MMM-YYYY
DIN/Aph ID: W0000 00 000000
JOIN: XXXX-XXXXX
LOT: XXXX-XXXXXY
EXP: DD-MMM-YYYY

Bag ID: XX

XXXX-XXXXXY-XX

304492

PRINCIPAL DISPLAY PANEL - 70 mL Cassette Label

idecabtagene vicleucel
Abecma™

NDC 59572-515-02
Genetically modified autologous T cells
FOR AUTOLOGOUS AND INTRAVENOUS USE ONLY

Suspension for IV Infusion
Rx Only

Acceptable Volume 30mL - 70mL per bag

Dosage: See prescribing information and Release for
Infusion Certificate (inside shipper).

Contains: 300 to 510 x 10^6 anti-BCMA02 CAR-positive T cells
in cryopreservative solution containing 5% DMSO USP.
Dose may be suspended in 1 or more infusion bag(s).

Do not use a leukodepleting filter or irradiate.

Not evaluated for infectious substances. Preservative free.

Store in vapor phase of liquid nitrogen (≤ -130°C).

Mfd by: Celgene Corporation, a Bristol-Myers Squibb Company
Summit, NJ 07901 USA
Phone: 1-888-805-4555
US License No. 2252

First: FIRST NAME
Last: LAST NAME
Date of birth: DD-MMM-YYYY
DIN/Aph ID: W0000 00 000000
JOIN: XXXX-XXXXX
LOT: XXXX-XXXXXY
EXP: DD-MMM-YYYY

Bag ID: XX

XXXX-XXXXXY-XX

304493

PRINCIPAL DISPLAY PANEL - 100 mL Bag Label

idecabtagene vicleucel
Abecma™

NDC 59572-515-03
Genetically modified autologous T cells
FOR AUTOLOGOUS AND INTRAVENOUS USE ONLY

Suspension for IV Infusion
Rx Only

Acceptable Volume 55mL - 100mL per bag

Dosage: See prescribing information and
Release for Infusion Certificate (inside shipper).

Contains: 300 to 510 x 10^6 anti-BCMA02
CAR-positive T cells in cryopreservative
solution containing 5% DMSO USP.
Dose may be suspended in 1 or more
infusion bag(s).

Do not use a leukodepleting filter
or irradiate.

Not evaluated for infectious substances.
Preservative free.

Store in vapor phase of liquid nitrogen
(≤ -130°C).

Mfd by: Celgene Corporation,
a Bristol-Myers Squibb Company
Summit, NJ 07901 USA
Phone: 1-888-805-4555
US License No. 2252

First: FIRST NAME
Last: LAST NAME
Date of birth: DD-MMM-YYYY
DIN/Aph ID: W0000 00 000000
JOIN: XXXX-XXXXX
LOT: XXXX-XXXXXY
EXP: DD-MMM-YYYY

Bag ID: XX

XXXX-XXXXXY-XX

304492

PRINCIPAL DISPLAY PANEL - 100 mL Cassette Label

idecabtagene vicleucel
Abecma™

NDC 59572-515-03
Genetically modified autologous T cells
FOR AUTOLOGOUS AND INTRAVENOUS USE ONLY

Suspension for IV Infusion
Rx Only

Acceptable Volume 55mL - 100mL per bag

Dosage: See prescribing information and Release for
Infusion Certificate (inside shipper).

Contains: 300 to 510 x 10^6 anti-BCMA02 CAR-positive T cells
in cryopreservative solution containing 5% DMSO USP.
Dose may be suspended in 1 or more infusion bag(s).

Do not use a leukodepleting filter or irradiate.

Not evaluated for infectious substances. Preservative free.

Store in vapor phase of liquid nitrogen (≤ -130°C).

Mfd by: Celgene Corporation, a Bristol-Myers Squibb Company
Summit, NJ 07901 USA
Phone: 1-888-805-4555
US License No. 2252

First: FIRST NAME
Last: LAST NAME
Date of birth: DD-MMM-YYYY
DIN/Aph ID: W0000 00 000000
JOIN: XXXX-XXXXX
LOT: XXXX-XXXXXY
EXP: DD-MMM-YYYY

Bag ID: XX

XXXX-XXXXXY-XX

304493